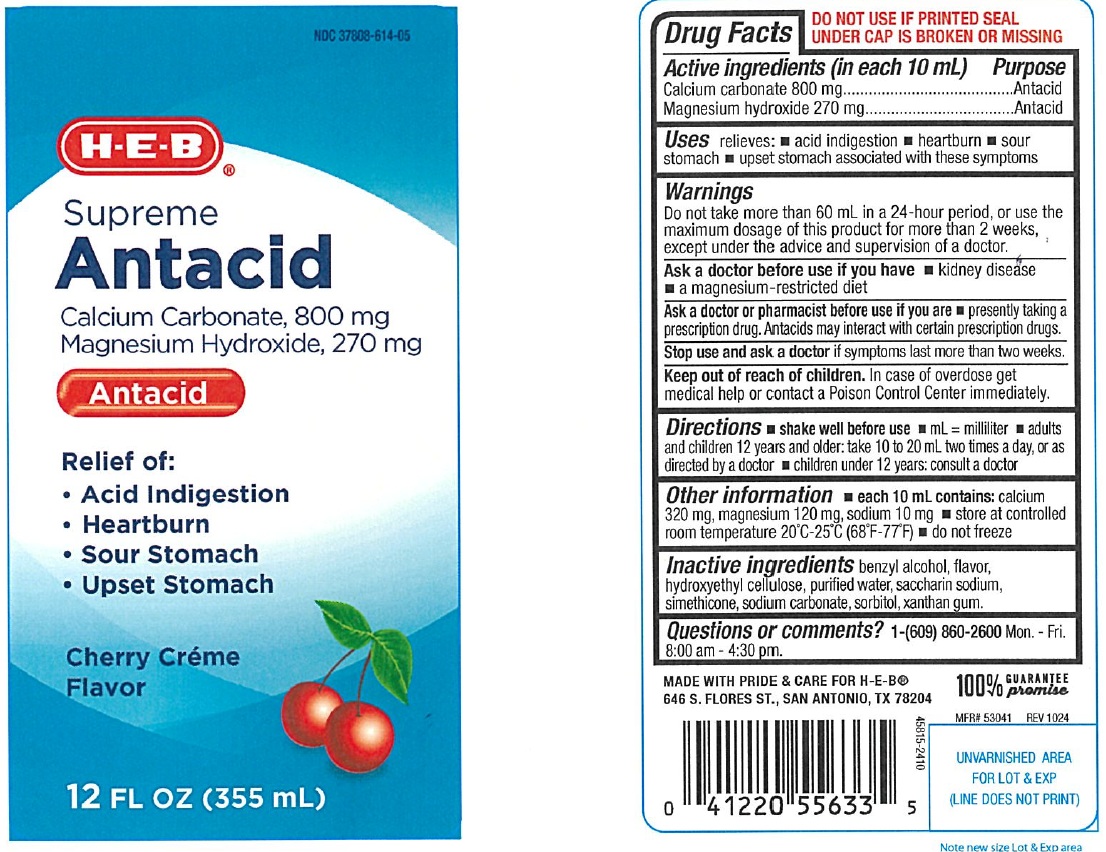 DRUG LABEL: Supreme Antacid
NDC: 37808-614 | Form: LIQUID
Manufacturer: H E B
Category: otc | Type: Human OTC Drug Label
Date: 20250314

ACTIVE INGREDIENTS: MAGNESIUM HYDROXIDE 270 mg/10 mL; CALCIUM CARBONATE 800 mg/10 mL
INACTIVE INGREDIENTS: BENZYL ALCOHOL; HYDROXYETHYL CELLULOSE (2000 MPA.S AT 1%); WATER; SACCHARIN SODIUM; SORBITOL; DIMETHICONE; SODIUM CARBONATE; XANTHAN GUM

Supreme Antacid Cherry

ACTIVE INGREDIENT (in each 10 mL)

Calcium carbonate 800 mg
Magnesium hydroxide 270 mg

PURPOSE

Antacid
Antacid

USE(S)

relieves:

- acid indigestion
- heartburn
- sour stomach
- upset stomach associated with these symptoms

WARNINGS

Do not take more than 60 mL in a 24-hour period, or use the maximum dosage of this product for more than 2 weeks, except under the advice and supervision of a doctor.

ASK A DOCTOR BEFORE USE IF YOU HAVE

- kidney disease
- a magnesium-restricted diet

ASK A DOCTOR OR PHARMACIST BEFORE USE IF YOU ARE

- presently taking a prescription drug. Antacids may interact with certain prescription drugs.

STOP USE AND ASK DOCTOR

if symptoms last more than two weeks

KEEP OUT OF REACH OF CHILDREN

In case of overdose get medical help or contact a Poison Control Center immediately.

DIRECTIONS

- shake well before use
- mL = milliliter
- adults and children 12 years and older: take 10 to 20 mL two times a day, or as directed by a doctor
- children under 12 years: consult a doctor

OTHER INFORMATION

- each 10 mL contains: calcium 320 mg, magnesium 120 mg, sodium 10 mg
- store at controlled room temperature 20ºC-25ºC (68º-77ºF)
- do not freeze

INACTIVE INGREDIENTS

benzyl alcohol, flavor, hydroxyethyl cellulose, purified water, saccharin sodium, simethicone, sodium carbonate, sorbitol, xanthan gum.

Questions or comments?

1-(609) 860-2600 Mon.- Fri. 8:00 am - 4:30 pm

PRINCIPAL DISPLAY PANEL

NDC 37808-614-05

H-E-B®

Supreme
Antacid

Calcium Carbonate, 800 mg

Magnesium Hydroxide, 270 mg

Antacid

Relief of:

- Acid Indigestion
- Heartburn
- Sour Stomach
- Upset Stomach

Cherry Creme
12 FL OZ (355 mL)